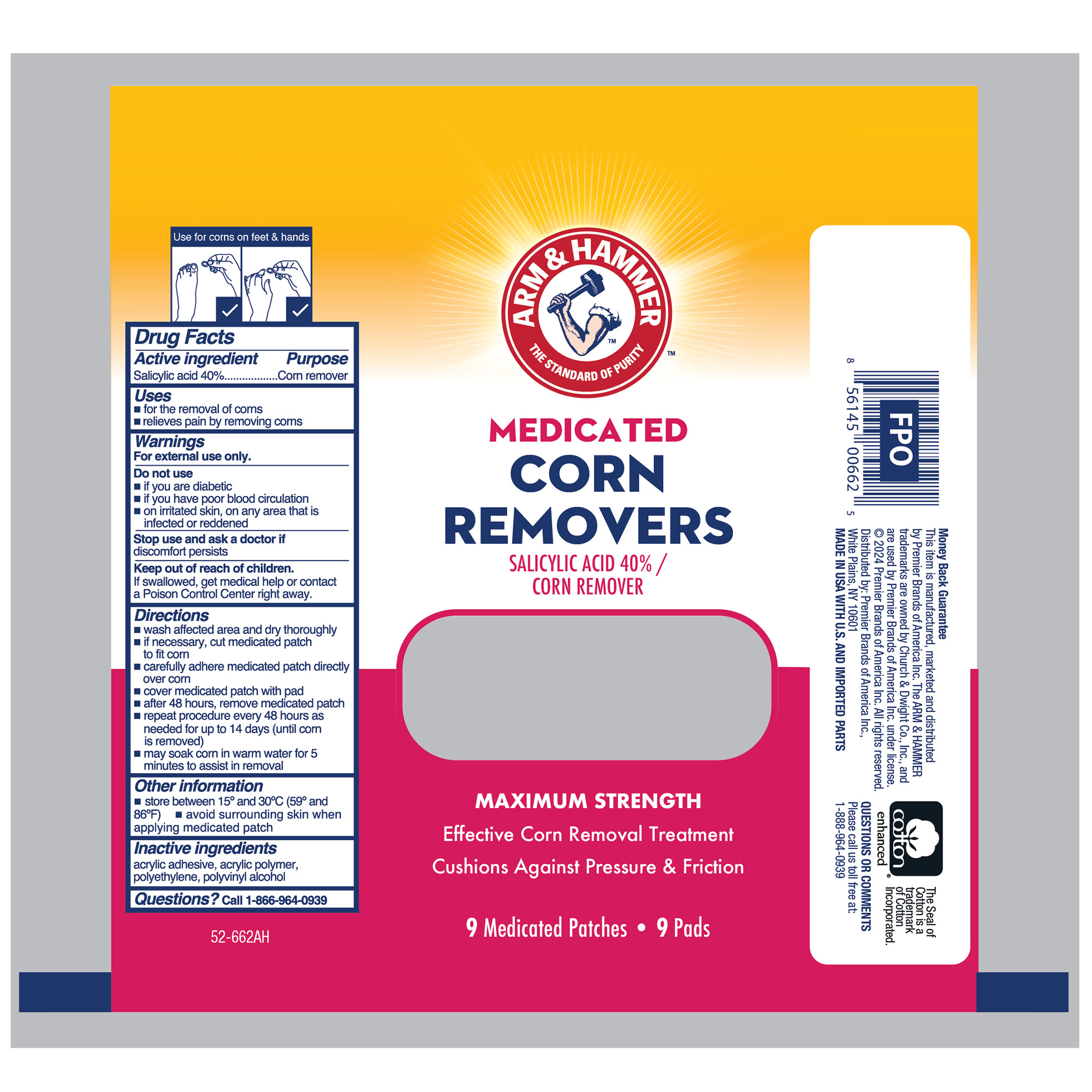 DRUG LABEL: Salicylic Acid
NDC: 56104-905 | Form: PATCH
Manufacturer: Premier Brands of America Inc.
Category: otc | Type: HUMAN OTC DRUG LABEL
Date: 20251230

ACTIVE INGREDIENTS: SALICYLIC ACID 400 mg/1 g
INACTIVE INGREDIENTS: POLYVINYL ALCOHOL, UNSPECIFIED; HIGH DENSITY POLYETHYLENE

Arm & Hammer Medicated Corn Removers

Active Ingredient

Salicylic Acid 40%

Purpose

Corn Remover

Uses

- for the removal of corns
- relieves pain by removing corns

Warnings

For External Use Only

Do not use

- if you are diabetic
- if you have poor blood circulation
- on irritated skin, on any area that is infected or reddened

Stop use and ask a doctor if

discomfort persists

Keep out of reach of children.

If swallowed, get medical help or contact a Poison Control Center right away.

Directions

- wash affected area and dry thoroughly
- if necessary, cut medicated patch to fit corn
- carefully adhere medicated patch directly over corn
- cover medicated patch with pad
- after 48 hours, remove medicated patch
- repeat procedure every 48 hours as needed for up to 14 days (until corn is removed)
- may soak corn in warm water for 5 minutes to assist in removal

Other information

- store between 15° and 30°C (59° and 86°F)
- avoid surrounding skin when applying medicated patch

Inactive ingredients

acrylic adhesive, acrylic polymer, polyethylene, polyvinyl alcohol

Questions?

call 1-866-964-0939

RECENT MAJOR CHANGES

.

Principal Display Panel

ARM & HAMMER

MEDICATED

CORN

REMOVERS

SALICYLIC ACID 40% /

CORN REMOVER

MAXIMUM STRENGTH

Effective Corn Removal Treatment

Cushions Against Pressure & Friction

9 Medicated Patches 9 Pads